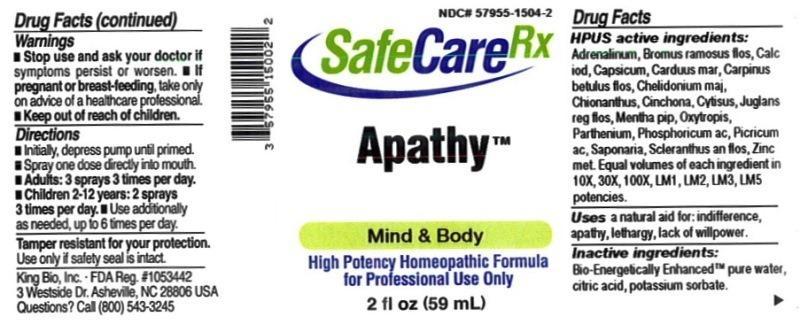 DRUG LABEL: Apathy
NDC: 57955-1504 | Form: LIQUID
Manufacturer: King Bio Inc.
Category: homeopathic | Type: HUMAN OTC DRUG LABEL
Date: 20150323

ACTIVE INGREDIENTS: EPINEPHRINE 10 [hp_X]/59 mL; BROMUS RAMOSUS FLOWER 10 [hp_X]/59 mL; CALCIUM IODIDE 10 [hp_X]/59 mL; CAPSICUM 10 [hp_X]/59 mL; MILK THISTLE 10 [hp_X]/59 mL; CARPINUS BETULUS FLOWERING TOP 10 [hp_X]/59 mL; CHELIDONIUM MAJUS 10 [hp_X]/59 mL; CHIONANTHUS VIRGINICUS BARK 10 [hp_X]/59 mL; CINCHONA OFFICINALIS BARK 10 [hp_X]/59 mL; CYTISUS SCOPARIUS FLOWERING TOP 10 [hp_X]/59 mL; JUGLANS REGIA FLOWERING TOP 10 [hp_X]/59 mL; MENTHA PIPERITA 10 [hp_X]/59 mL; OXYTROPIS LAMBERTII TOP 10 [hp_X]/59 mL; PARTHENIUM HYSTEROPHORUS 10 [hp_X]/59 mL; PHOSPHORIC ACID 10 [hp_X]/59 mL; PICRIC ACID 10 [hp_X]/59 mL; SAPONARIA OFFICINALIS ROOT 10 [hp_X]/59 mL; SCLERANTHUS ANNUUS FLOWERING TOP 10 [hp_X]/59 mL; ZINC 10 [hp_X]/59 mL
INACTIVE INGREDIENTS: WATER; ANHYDROUS CITRIC ACID; POTASSIUM SORBATE

Apathy™

Drug Facts

____________________________________________________________________________________________________________

HPUS active ingredients: Adrenalinum, Bromus ramosus, flos, Calcarea iodata, Capsicum annuum, Carduus marianus, Carpinus betulus, flos, Chelidonium majus, Chionanthus virginica, Cinchona officinalis, cytisus scoparius, Juglans regia, flos, Mentha piperita, Oxytropis lambertii, Parthenium, Phosphoricum acidum, Picricum acidum, Saponaria officinalis, Scleranthus annuus, flos, Zincum metallicum. Equal volumes of each ingredient in 10X, 30X, 100X, LM1, LM2, LM3, LM5 potencies.

INDICATIONS AND USAGE

Uses a natural aid for: indifference, apathy, lethargy, lack of willpower.

INACTIVE INGREDIENT

Inactive ingredients: Bio-Energetically Enhanced pure water, citric acid, potassium sorbate.

Warnings

- Stop use and ask your doctor if symptoms persist or worsen.
- If pregnant or breast-feeding, take only on advice of a healthcare professional.

- Keep out of reach of children.

Directions:

- Initially, depress pump until primed.
- Spray one dose directly into mouth.
- Adults: 3 sprays 3 times per day.
- Children 2-12 years: 2 sprays 3 times per day.
- Use additionally as needed, up to 6 times per day.

OTHER SAFETY INFORMATION

Tamper resistant for your protection. Use only if safety seal is intact.

PURPOSE

Uses a natural aid for:

- indifference
- apathy
- lethargy
- lack of willpower